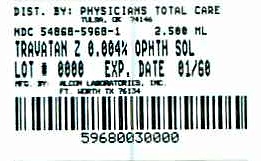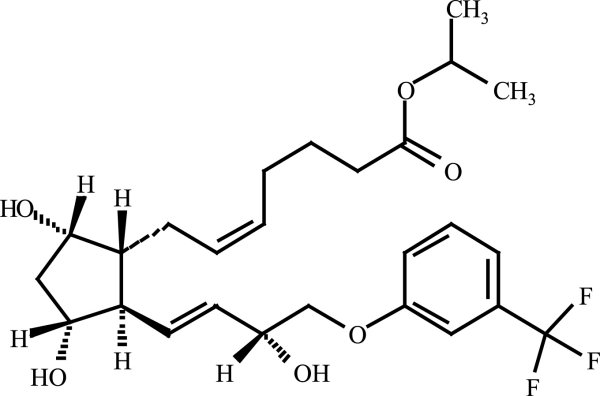 DRUG LABEL: Travatan Z
NDC: 54868-5968 | Form: SOLUTION
Manufacturer: Physicians Total Care, Inc.
Category: prescription | Type: HUMAN PRESCRIPTION DRUG LABEL
Date: 20110720

ACTIVE INGREDIENTS: TRAVOPROST 0.04 mg/1 mL
INACTIVE INGREDIENTS: POLYOXYL 40 CASTOR OIL; BORIC ACID; PROPYLENE GLYCOL; SORBITOL; ZINC CHLORIDE; SODIUM HYDROXIDE; HYDROCHLORIC ACID; WATER

HIGHLIGHTS OF PRESCRIBING INFORMATION

These highlights do not include all the information needed to use TRAVATAN Z® (travoprost ophthalmic solution) 0.004% safely and effectively. See full prescribing information for TRAVATAN Z®.
TRAVATAN Z® (travoprost ophthalmic solution) 0.004%
Initial U.S. Approval: 2001

1 INDICATIONS AND USAGE

TRAVATAN Z® is a prostaglandin analog indicated for the reduction of elevated intraocular pressure in patients with open-angle glaucoma or ocular hypertension. (1)

2 DOSAGE AND ADMINISTRATION

One drop in the affected eye(s) once daily in the evening. (2)

3 DOSAGE FORMS AND STRENGTHS

Solution containing 0.04 mg/mL travoprost ophthalmic solution. (3)

5 WARNINGS AND PRECAUTIONS

Pigmentation.

Pigmentation of the iris, periorbital tissue (eyelid) and eyelashes can occur. Iris pigmentation likely to be permanent. (5.1)

Eyelash Changes.

Gradual change to eyelashes including increased length, thickness and number of lashes. Usually reversible. (5.2)

6 ADVERSE REACTIONS

Most common adverse reaction (30% to 50%) is conjunctival hyperemia. (6.1)

To report SUSPECTED ADVERSE REACTIONS, contact Alcon Laboratories Inc. at 1-800-757-9195 or FDA at 1-800-FDA-1088 or www.fda.gov/medwatch.

8 USE IN SPECIFIC POPULATIONS

Use in pediatric patients below the age of 16 years is not recommended because of potential safety concerns related to increased pigmentation following long-term chronic use. (8.4)

FULL PRESCRIBING INFORMATION

1 INDICATIONS AND USAGE

TRAVATAN Z® (travoprost ophthalmic solution) 0.004% is indicated for the reduction of elevated intraocular pressure in patients with open-angle glaucoma or ocular hypertension.

2 DOSAGE AND ADMINISTRATION

The recommended dosage is one drop in the affected eye(s) once daily in the evening. TRAVATAN Z® (travoprost ophthalmic solution) should not be administered more than once daily since it has been shown that more frequent administration of prostaglandin analogs may decrease the intraocular pressure lowering effect.

Reduction of the intraocular pressure starts approximately 2 hours after the first administration with maximum effect reached after 12 hours.

TRAVATAN Z® may be used concomitantly with other topical ophthalmic drug products to lower intraocular pressure. If more than one topical ophthalmic drug is being used, the drugs should be administered at least five (5) minutes apart.

3 DOSAGE FORMS AND STRENGTHS

Ophthalmic solution containing travoprost 0.04 mg/mL.

4 CONTRAINDICATIONS

None

5 WARNINGS AND PRECAUTIONS

5.1 Pigmentation

Travoprost ophthalmic solution has been reported to cause changes to pigmented tissues. The most frequently reported changes have been increased pigmentation of the iris, periorbital tissue (eyelid) and eyelashes. Pigmentation is expected to increase as long as travoprost is administered. The pigmentation change is due to increased melanin content in the melanocytes rather than to an increase in the number of melanocytes. After discontinuation of travoprost, pigmentation of the iris is likely to be permanent, while pigmentation of the periorbital tissue and eyelash changes have been reported to be reversible in some patients. Patients who receive treatment should be informed of the possibility of increased pigmentation. The long term effects of increased pigmentation are not known.

Iris color change may not be noticeable for several months to years. Typically, the brown pigmentation around the pupil spreads concentrically towards the periphery of the iris and the entire iris or parts of the iris become more brownish. Neither nevi nor freckles of the iris appear to be affected by treatment. While treatment with TRAVATAN Z® (travoprost ophthalmic solution) 0.004% can be continued in patients who develop noticeably increased iris pigmentation, these patients should be examined regularly. (see PATIENT COUNSELING INFORMATION, 17.1).

5.2 Eyelash Changes

TRAVATAN Z® may gradually change eyelashes and vellus hair in the treated eye. These changes include increased length, thickness, and number of lashes. Eyelash changes are usually reversible upon discontinuation of treatment.

5.3 Intraocular Inflammation

TRAVATAN Z® should be used with caution in patients with active intraocular inflammation (e.g., uveitis) because the inflammation may be exacerbated.

5.4 Macular Edema

Macular edema, including cystoid macular edema, has been reported during treatment with travoprost ophthalmic solution. TRAVATAN Z® should be used with caution in aphakic patients, in pseudophakic patients with a torn posterior lens capsule, or in patients with known risk factors for macular edema.

5.5 Angle-closure, Inflammatory or Neovascular Glaucoma

TRAVATAN Z® has not been evaluated for the treatment of angle-closure, inflammatory or neovascular glaucoma.

5.6 Bacterial Keratitis

There have been reports of bacterial keratitis associated with the use of multiple-dose containers of topical ophthalmic products. These containers had been inadvertently contaminated by patients who, in most cases, had a concurrent corneal disease or a disruption of the ocular epithelial surface (see PATIENT COUNSELING INFORMATION, 17.3).

5.7 Use with Contact Lenses

Contact lenses should be removed prior to instillation of TRAVATAN Z® and may be reinserted 15 minutes following its administration.

6 ADVERSE REACTIONS

6.1 Clinical Studies Experience

Because clinical studies are conducted under widely varying conditions, adverse reaction rates observed in the clinical studies of a drug cannot be directly compared to rates in the clinical studies of another drug and may not reflect the rates observed in practice.

The most common adverse reaction observed in controlled clinical studies with TRAVATAN® (travoprost ophthalmic solution) 0.004% and TRAVATAN Z® (travoprost ophthalmic solution) 0.004% was ocular hyperemia which was reported in 30 to 50% of patients. Up to 3% of patients discontinued therapy due to conjunctival hyperemia. Ocular adverse reactions reported at an incidence of 5 to 10% in these clinical studies included decreased visual acuity, eye discomfort, foreign body sensation, pain and pruritus.

Ocular adverse reactions reported at an incidence of 1 to 4% in clinical studies with TRAVATAN® or TRAVATAN Z® included abnormal vision, blepharitis, blurred vision, cataract, conjunctivitis, corneal staining, dry eye, iris discoloration, keratitis, lid margin crusting, ocular inflammation, photophobia, subconjunctival hemorrhage and tearing.

Nonocular adverse reactions reported at an incidence of 1 to 5% in these clinical studies were allergy, angina pectoris, anxiety, arthritis, back pain, bradycardia, bronchitis, chest pain, cold/flu syndrome, depression, dyspepsia, gastrointestinal disorder, headache, hypercholesterolemia, hypertension, hypotension, infection, pain, prostate disorder, sinusitis, urinary incontinence and urinary tract infections.

8 USE IN SPECIFIC POPULATIONS

8.1 Pregnancy

Pregnancy Category C

Teratogenic effects: Travoprost was teratogenic in rats, at an intravenous (IV) dose up to 10 mcg/kg/day (250 times the maximal recommended human ocular dose (MRHOD), evidenced by an increase in the incidence of skeletal malformations as well as external and visceral malformations, such as fused sternebrae, domed head and hydrocephaly. Travoprost was not teratogenic in rats at IV doses up to 3 mcg/kg/day (75 times the MRHOD), or in mice at subcutaneous doses up to 1 mcg/kg/day (25 times the MRHOD). Travoprost produced an increase in post-implantation losses and a decrease in fetal viability in rats at IV doses > 3 mcg/kg/day (75 times the MRHOD) and in mice at subcutaneous doses > 0.3 mcg/kg/day (7.5 times the MRHOD).

In the offspring of female rats that received travoprost subcutaneously from Day 7 of pregnancy to lactation Day 21 at doses of = 0.12 mcg/kg/day (3 times the MRHOD), the incidence of postnatal mortality was increased, and neonatal body weight gain was decreased. Neonatal development was also affected, evidenced by delayed eye opening, pinna detachment and preputial separation, and by decreased motor activity.

There are no adequate and well-controlled studies of TRAVATAN Z® (travoprost ophthalmic solution) 0.004% administration in pregnant women. Because animal reproductive studies are not always predictive of human response, TRAVATAN Z® should be administered during pregnancy only if the potential benefit justifies the potential risk to the fetus.

8.3 Nursing Mothers

A study in lactating rats demonstrated that radiolabeled travoprost and/or its metabolites were excreted in milk. It is not known whether this drug or its metabolites are excreted in human milk. Because many drugs are excreted in human milk, caution should be exercised when TRAVATAN Z® is administered to a nursing woman.

8.4 Pediatric Use

Use in pediatric patients below the age of 16 years is not recommended because of potential safety concerns related to increased pigmentation following long-term chronic use.

8.5 Geriatric Use

No overall clinical differences in safety or effectiveness have been observed between elderly and other adult patients.

8.6 Hepatic and Renal Impairment

Travoprost ophthalmic solution 0.004% has been studied in patients with hepatic impairment and also in patients with renal impairment. No clinically relevant changes in hematology, blood chemistry, or urinalysis laboratory data were observed in these patients.

11 DESCRIPTION

Travoprost is a synthetic prostaglandin F analogue. Its chemical name is [1R-[1α(Z),2β(1E,3R*),3α,5α]]-7-[3,5-Dihydroxy-2-[3-hydroxy-4-[3-(trifluoromethyl) phenoxy]-1-butenyl]cyclopentyl]-5-heptenoic acid, 1-methylethylester. It has a molecular formula of C26H35F3O6 and a molecular weight of 500.55. The chemical structure of travoprost is:

Travoprost is a clear, colorless to slightly yellow oil that is very soluble in acetonitrile, methanol, octanol, and chloroform. It is practically insoluble in water.

TRAVATAN Z® (travoprost ophthalmic solution) 0.004% is supplied as sterile, buffered aqueous solution of travoprost with a pH of approximately 5.7 and an osmolality of approximately 290 mOsmol/kg.

TRAVATAN Z® contains Active: travoprost 0.04 mg/mL; Inactives: polyoxyl 40 hydrogenated castor oil, sofZia® (boric acid, propylene glycol, sorbitol, zinc chloride), sodium hydroxide and/or hydrochloric acid (to adjust pH) and purified water, USP. Preserved in the bottle with an ionic buffered system, sofZia®.

12 CLINICAL PHARMACOLOGY

12.1 Mechanism of Action

Travoprost free acid, a prostaglandin analog is a selective FP prostanoid receptor agonist which is believed to reduce intraocular pressure by increasing uveoscleral outflow. The exact mechanism of action is unknown at this time.

12.3 Pharmacokinetics

Travoprost is absorbed through the cornea and is hydrolyzed to the active free acid. Data from four multiple dose pharmacokinetic studies (totaling 107 subjects) have shown that plasma concentrations of the free acid are below 0.01 ng/ml (the quantitation limit of the assay) in two-thirds of the subjects. In those individuals with quantifiable plasma concentrations (N=38), the mean plasma Cmax was 0.018 ± 0.007 ng/ml (ranged 0.01 to 0.052 ng/mL) and was reached within 30 minutes. From these studies, travoprost is estimated to have a plasma half-life of 45 minutes. There was no difference in plasma concentrations between Days 1 and 7, indicating steady-state was reached early and that there was no significant accumulation.

Travoprost, an isopropyl ester prodrug, is hydrolyzed by esterases in the cornea to its biologically active free acid. Systemically, travoprost free acid is metabolized to inactive metabolites via beta-oxidation of the α(carboxylic acid) chain to give the 1,2-dinor and 1,2,3,4-tetranor analogs, via oxidation of the 15-hydroxyl moiety, as well as via reduction of the 13,14 double bond.

The elimination of travoprost free acid from plasma was rapid and levels were generally below the limit of quantification within one hour after dosing. The terminal elimination half-life of travoprost free acid was estimated from fourteen subjects and ranged from 17 minutes to 86 minutes with the mean half-life of 45 minutes. Less than 2% of the topical ocular dose of travoprost was excreted in the urine within 4 hours as the travoprost free acid.

13 NONCLINICAL TOXICOLOGY

13.1 Carcinogenesis, Mutagenesis, Impairment of Fertility

Two-year carcinogenicity studies in mice and rats at subcutaneous doses of 10, 30, or 100 mcg/kg/day did not show any evidence of carcinogenic potential. However, at 100 mcg/kg/day, male rats were only treated for 82 weeks, and the maximum tolerated dose (MTD) was not reached in the mouse study. The high dose (100 mcg/kg) corresponds to exposure levels over 400 times the human exposure at the maximum recommended human ocular dose (MRHOD) of 0.04 mcg/kg, based on plasma active drug levels.

Travoprost was not mutagenic in the Ames test, mouse micronucleus test or rat chromosome aberration assay. A slight increase in the mutant frequency was observed in one of two mouse lymphoma assays in the presence of rat S-9 activation enzymes.

Travoprost did not affect mating or fertility indices in male or female rats at subcutaneous doses up to 10 mcg/kg/day [250 times the maximum recommended human ocular dose of 0.04 mcg/kg/day on a mcg/kg basis (MRHOD)]. At 10 mcg/kg/day, the mean number of corpora lutea was reduced, and the post-implantation losses were increased. These effects were not observed at 3 mcg/kg/day (75 times the MRHOD).

14 CLINICAL STUDIES

In clinical studies, patients with open-angle glaucoma or ocular hypertension and baseline pressure of 25-27 mmHg who were treated with TRAVATAN® (travoprost ophthalmic solution) 0.004% or TRAVATAN Z® (travoprost ophthalmic solution) 0.004% dosed once-daily in the evening demonstrated 7-8 mmHg reductions in intraocular pressure. In subgroup analyses of these studies, mean IOP reduction in black patients was up to 1.8 mmHg greater than in non-black patients. It is not known at this time whether this difference is attributed to race or to heavily pigmented irides.

In a multi-center, randomized, controlled trial, patients with mean baseline intraocular pressure of 24-26 mmHg on TIMOPTIC* 0.5% BID who were treated with TRAVATAN® (travoprost ophthalmic solution) 0.004% dosed QD adjunctively to TIMOPTIC* 0.5% BID demonstrated 6-7 mmHg reductions in intraocular pressure.

16 HOW SUPPLIED/STORAGE AND HANDLING

TRAVATAN Z® (travoprost ophthalmic solution) 0.004% is a sterile, isotonic, buffered, preserved, aqueous solution of travoprost (0.04 mg/mL) supplied in Alcon's oval DROP-TAINER® package system.

TRAVATAN Z® is supplied as a 2.5 mL solution in a 4 mL and a 5 mL solution in a 7.5 mL natural polypropylene dispenser bottle with a natural polypropylene dropper tip and a turquoise polypropylene or high density polyethylene overcap. Tamper evidence is provided with a shrink band around the closure and neck area of the package.

2.5 mL fill NDC 54868-5968-1

5 mL fill NDC 54868-5968-0

Storage: Store at 2° - 25°C (36° - 77°F).

17 PATIENT COUNSELING INFORMATION

17.1 Potential for Pigmentation

Patients should be advised about the potential for increased brown pigmentation of the iris, which may be permanent. Patients should also be informed about the possibility of eyelid skin darkening, which may be reversible after discontinuation of TRAVATAN Z® (travoprost ophthalmic solution) 0.004%.

17.2 Potential for Eyelash Changes

Patients should also be informed of the possibility of eyelash and vellus hair changes in the treated eye during treatment with TRAVATAN Z®. These changes may result in a disparity between eyes in length, thickness, pigmentation, number of eyelashes or vellus hairs, and/or direction of eyelash growth. Eyelash changes are usually reversible upon discontinuation of treatment.

17.3 Handling the Container

Patients should be instructed to avoid allowing the tip of the dispensing container to contact the eye, surrounding structures, fingers, or any other surface in order to avoid contamination of the solution by common bacteria known to cause ocular infections. Serious damage to the eye and subsequent loss of vision may result from using contaminated solutions.

17.4 When to Seek Physician Advice

Patients should also be advised that if they develop an intercurrent ocular condition (e.g., trauma or infection), have ocular surgery, or develop any ocular reactions, particularly conjunctivitis and eyelid reactions, they should immediately seek their physician's advice concerning the continued use of TRAVATAN Z®.

17.5 Use with Contact Lenses

Contact lenses should be removed prior to instillation of TRAVATAN® and may be reinserted 15 minutes following its administration.

17.6 Use with Other Ophthalmic Drugs

If more than one topical ophthalmic drug is being used, the drugs should be administered at least five (5) minutes between applications.

Rx Only

U.S. Patent Nos. 5,631,287; 5,889,052; 6,011,062; 6,235,781; 6,503,497 and 6,849,283

* TIMOPTIC is a registered trademark of Merck & Co., Inc.

ALCON®

ALCON LABORATORIES, INC.

Fort Worth, Texas 76134 USA

© 2006, 2010 Alcon, Inc.

Additional barcode labeling by:
Physicians Total Care, Inc.
Tulsa, OK 74146

PRINCIPAL DISPLAY PANEL

NDC 54868-5968-1

Rx Only

TRAVATAN Z®

(travoprost ophthalmic

solution) 0.004%

2.5 mL

STERILE